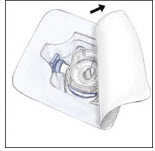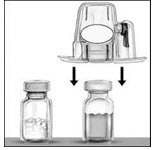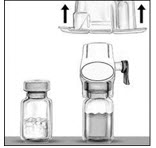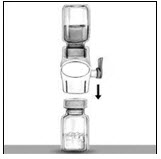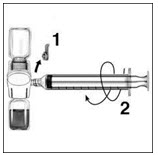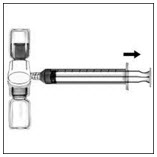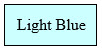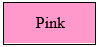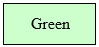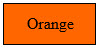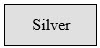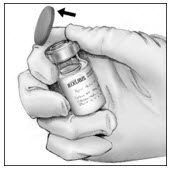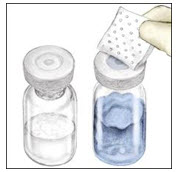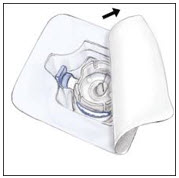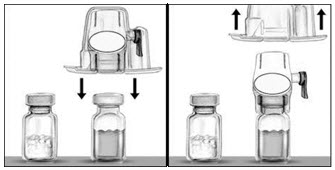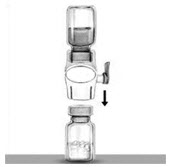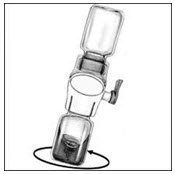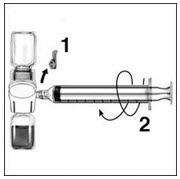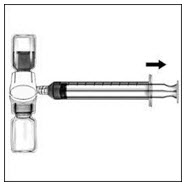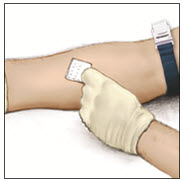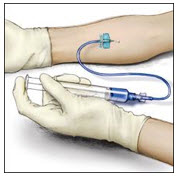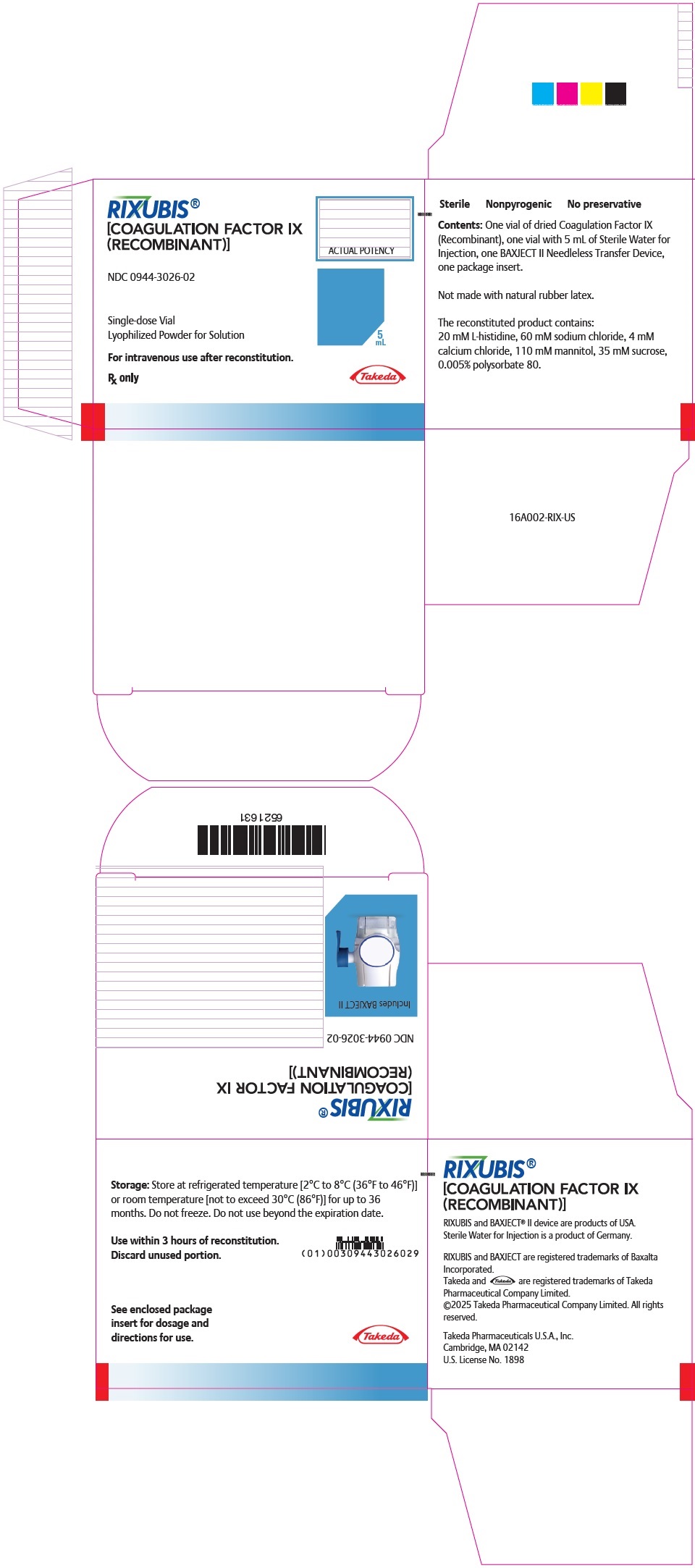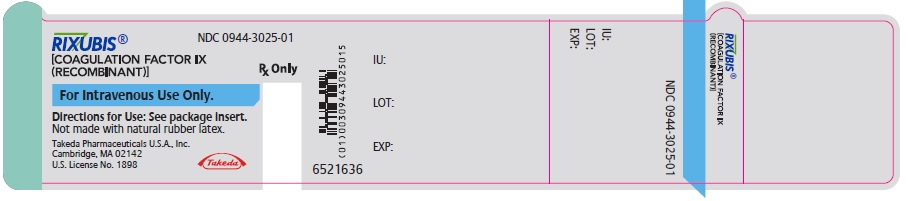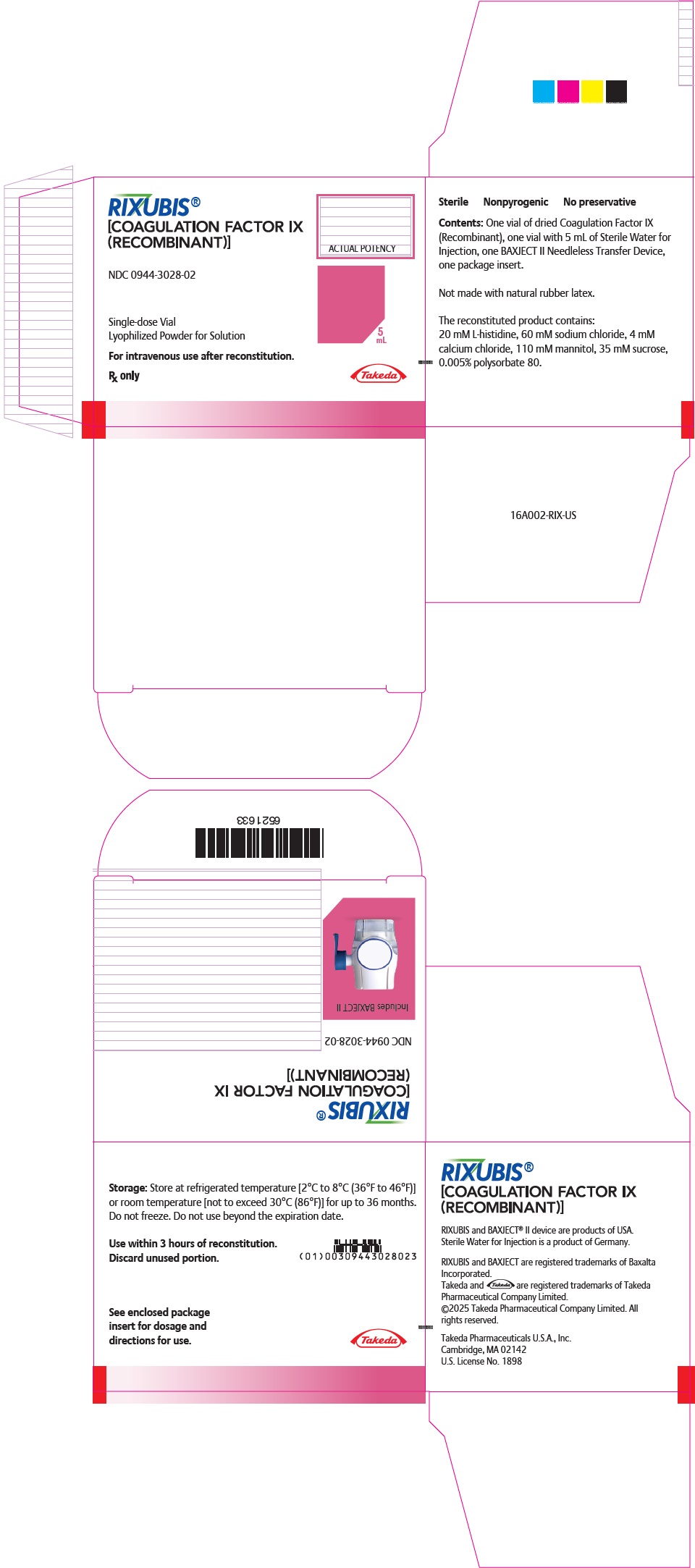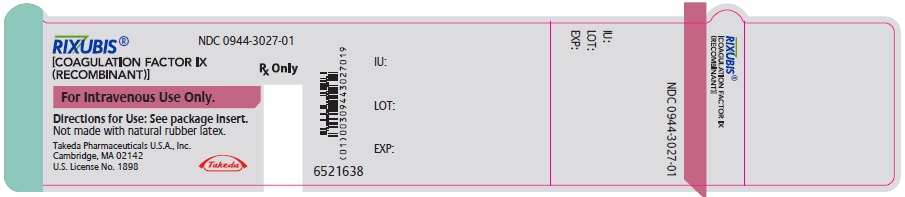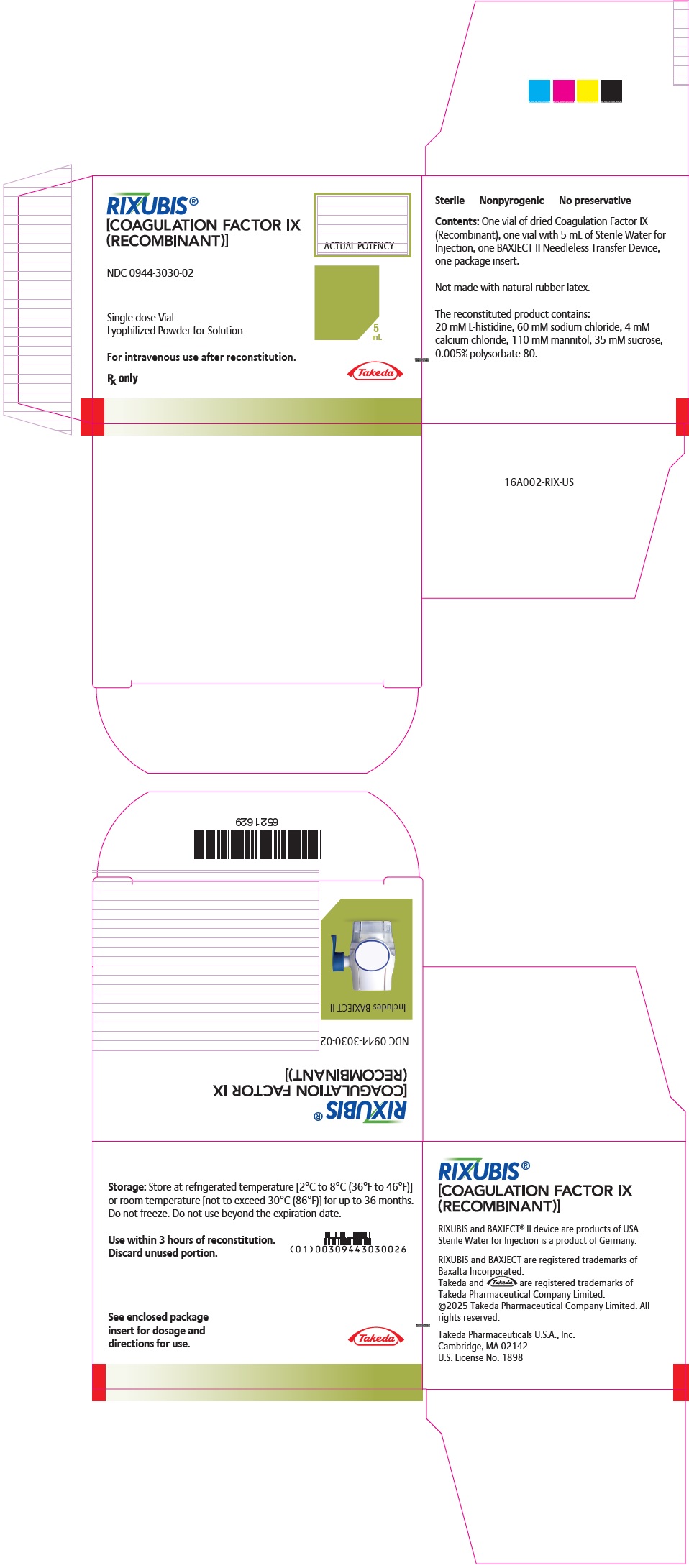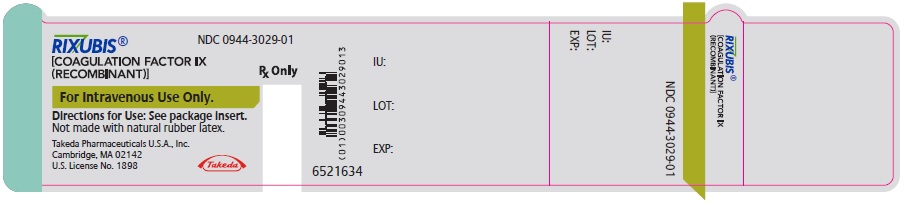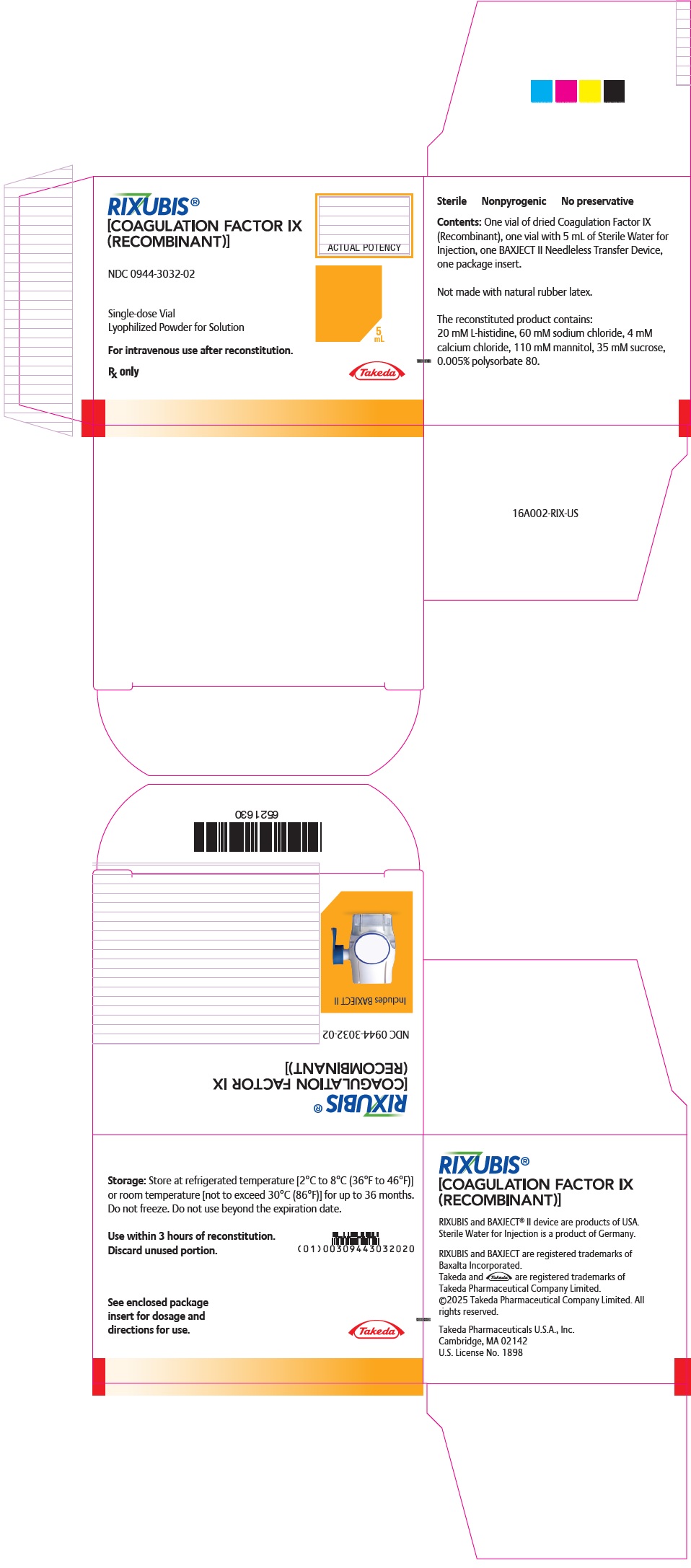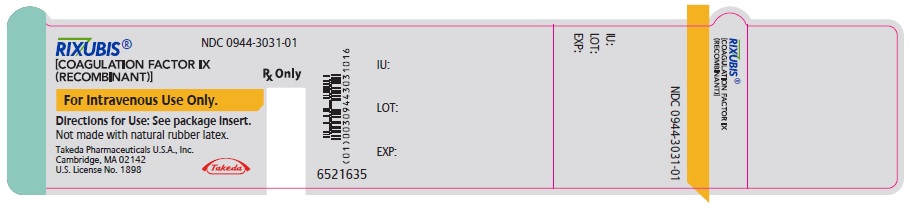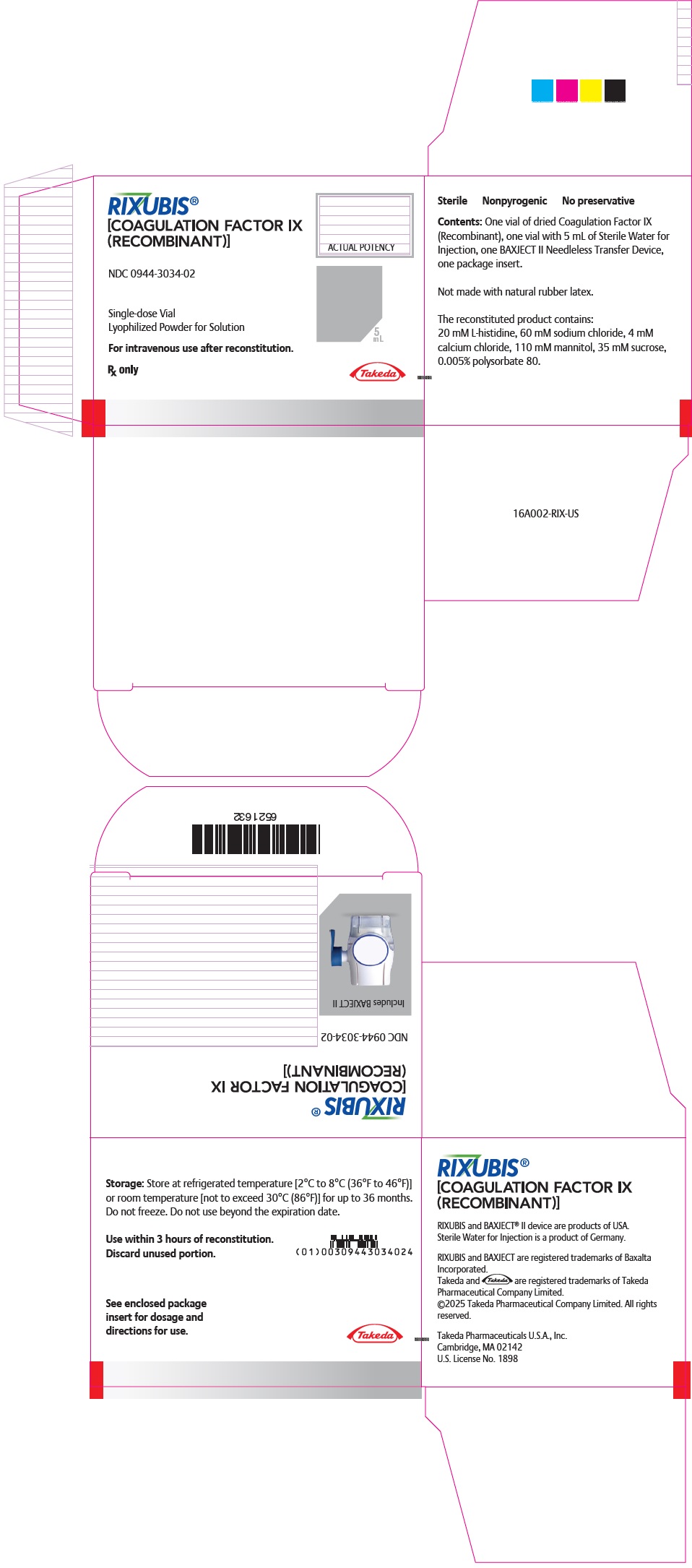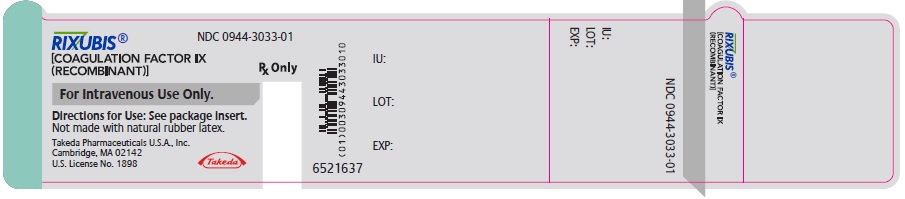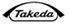 DRUG LABEL: RIXUBIS
NDC: 0944-3026 | Form: KIT | Route: INTRAVENOUS
Manufacturer: Takeda Pharmaceuticals America, Inc.
Category: other | Type: PLASMA DERIVATIVE
Date: 20250407

ACTIVE INGREDIENTS: COAGULATION FACTOR IX RECOMBINANT HUMAN 250 [iU]/5 mL
INACTIVE INGREDIENTS: HISTIDINE; SODIUM CHLORIDE; CALCIUM CHLORIDE; MANNITOL; SUCROSE; POLYSORBATE 80; WATER 5 mL/5 mL

HIGHLIGHTS OF PRESCRIBING INFORMATION

These highlights do not include all the information needed to use RIXUBIS® safely and effectively. See full prescribing information for RIXUBIS.
RIXUBIS [Coagulation Factor IX (Recombinant)]
For Intravenous Injection, Lyophilized Powder for Solution
Initial U.S. Approval: 2013

1 INDICATIONS AND USAGE

RIXUBIS (Coagulation Factor IX [Recombinant]) is an antihemophilic factor indicated in adults and children with hemophilia B for:

- On-demand treatment and control of bleeding episodes
- Perioperative management of bleeding
- Routine prophylaxis to reduce the frequency of bleeding episodes.

RIXUBIS is not indicated for induction of immune tolerance in patients with Hemophilia B. (1)

2 DOSAGE AND ADMINISTRATION

For intravenous use after reconstitution only. (2)

On-demand treatment and control of bleeding episodes and perioperative management of bleeding:

- One international unit of RIXUBIS per kg of body weight increases the circulating activity of factor IX by 0.7 international units/dL for patients <12 years of age and 0.9 international units/dL for patients ≥12 years of age. (2.1)

Initial Dose:

- Required international units = body weight (kg) × desired factor IX increase (% of normal or IU/dL) × reciprocal of observed recovery (IU/kg per IU/dL). (2.1)
- The maintenance dose depends on the type of bleed or surgery, the intensity of the hemostatic challenge, and number of days until adequate wound healing is achieved. (2.2)

Routine prophylaxis:

- Patients <12 years of age: 60 to 80 international units per kg twice weekly.
- Patients ≥12 years of age: 40 to 60 international units per kg twice weekly. (2.1)

3 DOSAGE FORMS AND STRENGTHS

RIXUBIS is available as a lyophilized powder in single-dose vials containing nominally 250, 500, 1000, 2000, or 3000 international units. (3)

4 CONTRAINDICATIONS

Do not use in patients with:

- Known hypersensitivity to RIXUBIS or its excipients including hamster protein. (4)
- Disseminated intravascular coagulation (DIC). (4)
- Signs of fibrinolysis. (4)

5 WARNINGS AND PRECAUTIONS

- Hypersensitivity reactions, including anaphylaxis, may occur. Should symptoms occur, discontinue RIXUBIS and administer appropriate treatment. Patients may also develop hypersensitivity to hamster (CHO) protein, which is present in trace amounts in the product. (5.1)
- Development of neutralizing antibodies (inhibitors) to RIXUBIS may occur. If expected factor IX activity plasma levels are not attained, or if bleeding is not controlled with an appropriate dose, perform an assay that measures factor IX inhibitor concentration. (5.2)
- Nephrotic syndrome has been reported following immune tolerance induction with factor IX products in hemophilia B patients with factor IX inhibitors. (5.3)
- The use of factor IX-containing products has been associated with the development of thromboembolic complications. (5.4)

6 ADVERSE REACTIONS

Common adverse reactions observed in >1% of subjects in clinical trials were: dysgeusia, pain in extremity, and positive test for furin antibody. (6.1)

To report SUSPECTED ADVERSE REACTIONS, contact Takeda Pharmaceuticals U.S.A., Inc. at 1-877-TAKEDA-7 (1-877-825-3327) or FDA at 1-800-FDA-1088 or www.fda.gov/medwatch.

8 USE IN SPECIFIC POPULATIONS

Pediatric Use: A 22% lower recovery has been observed in pediatric patients (<12 years, n=23). Clearance (based on per kg body weight) was 30% (6-12 years) and 59% (<6 years) higher in children than adults. Dose adjustment is needed. (2.1, 8.4)

FULL PRESCRIBING INFORMATION

1 INDICATIONS AND USAGE

RIXUBIS® (Coagulation Factor IX [Recombinant]) is an antihemophilic factor indicated in adults and children with hemophilia B for:

- On-demand treatment and control of bleeding episodes
- Perioperative management of bleeding
- Routine prophylaxis to reduce the frequency of bleeding episodes.

RIXUBIS is not indicated for induction of immune tolerance in patients with hemophilia B [see Warnings and Precautions (5.3)].

2 DOSAGE AND ADMINISTRATION

For intravenous use after reconstitution only.

- Each vial of RIXUBIS has the recombinant Factor IX (rFIX) potency in international units stated on the vial.
- Initiate treatment under the supervision of a physician experienced in the treatment of hemophilia.
- Dosage and duration of treatment with RIXUBIS depend on the severity of factor IX deficiency, the location and extent of bleeding, the patient's clinical condition, age, and pharmacokinetic parameters of factor IX, such as incremental recovery and half-life.
- Dosing of RIXUBIS may differ from that of plasma-derived factor IX products [see Clinical Pharmacology (12)]. Subjects at the low end of the observed factor IX recovery range may require dose adjustment of RIXUBIS.
- Monitor patients using a factor IX activity assay to ensure that the desired factor IX activity plasma level has been attained. If necessary, adjust the dose and the frequency of repeated infusions as appropriate.
- Evaluate the patient for the development of factor IX inhibitors if the expected factor IX activity plasma levels are not attained or if bleeding is not controlled with an appropriate dose [see Warnings and Precautions (5.2)].

2.1 Dosing Guidelines

Calculating Initial Dose

The initial dose of RIXUBIS is calculated based on the empirical finding that one international unit of RIXUBIS per kg body weight is expected to increase the circulating level of factor IX by 0.7 international units/dL of plasma (0.7% of normal) for patients <12 years of age and by 0.9 international units/dL of plasma (0.9% of normal) in patients ≥12 years of age.

A guide for calculating the initial dose of RIXUBIS for treatment of bleeding episodes is as follows:

Initial Dose = body weight (kg) × desired factor IX increase (% of normal or IU/dL) × reciprocal of observed recovery (IU/kg per IU/dL)

Incremental Recovery in Previously Treated Patients (PTPs)

Base the calculation of the dose on the patient's individual incremental recovery using serial factor IX activity assays, due to the wide range of inter-individual differences in incremental recovery. Titrate the dose based on the patient's clinical response and individual pharmacokinetics, in particular incremental recovery and half-life.

Patients <12 Years of Age

On average, a 22% lower recovery has been observed in pediatric patients (<12 years, n=23). For an incremental recovery of 0.7 international units/dL of plasma (0.7% of normal), the dose is calculated as follows:

Dose (international units) = body weight (kg) × desired factor IX increase (% of normal or IU/dL) × 1.4 dL/kg

Example (assuming patient's baseline factor IX level is <1% of normal)

1. A dose of 1500 international units of RIXUBIS, administered to a 20 kg patient should be expected to result in a peak post-infusion factor IX increase of 1500 international units × {[0.7 IU/dL]/[IU/kg]}/[20 kg] = 53.6 international units/dL (53.6% of normal).

Patients ≥12 Years of Age

For an incremental recovery of 0.9 international units/dL of plasma (0.9% of normal), the dose is calculated as follows:

Dose (international units) = body weight (kg) × desired factor IX increase (% of normal or IU/dL) × 1.1 dL/kg

Examples (assuming patient's baseline factor IX level is <1% of normal):

1. A dose of 4550 international units of RIXUBIS, administered to a 70 kg patient, should be expected to result in a peak post-infusion factor IX increase of 4550 international units × {[0.9 IU/dL]/[IU/kg]}/[70 kg] = 58.5 international units/dL (58.5 % of normal).
2. A peak level of 70% is required in a 60 kg patient. The appropriate dose would be 60 kg × 70 international units/dL/{[0.9 IU/dL]/[IU/kg]} = 4667 international units.

2.2 On-demand Treatment and Control of Bleeding Episodes and Perioperative Management of Bleeding

A guide for dosing RIXUBIS in the on-demand treatment and control of bleeding episodes and perioperative management of bleeding is provided in Table 1 and Table 2, respectively. Ensure the factor IX activity level is achieved and maintained in the corresponding period.

Table 1 Dosing for On-demand Treatment and Control of Bleeding Episodes^1
Type of Bleeding Episodes | Circulating Factor IX Level Required (% or IU/dL) | Dosing Interval (hours) | Duration of Therapy (days)
Minor Uncomplicated hemarthrosis, superficial muscular or soft tissue | 20-30 | 12-24 | At least 1 day, until healing is achieved
Moderate Intramuscular or soft tissue with dissection, mucous membranes, hematuria | 25-50 | 12-24 | 2-7 days, until bleeding stops, and healing is achieved
Major Pharyngeal, retropharyngeal, retroperitoneal, CNS | 50-100 | 12-24 | 7-10 days, until bleeding stops, and healing is achieved
Adapted from Roberts and Eberst^1

Table 2 Dosing for Perioperative Management of Bleeding
Type of Surgery | Circulating Factor IX Level Required (% or IU/dL) | Dosing Interval (hours) | Duration of Therapy (days)
Minor e.g., tooth extraction | 30-60 | 24 | At least 1 day, until healing is achieved
Major e.g., intracranial, intraabdominal, intrathoracic, joint replacement | 80-100 | 8-24 | 7-10 days, until bleeding stops and healing is achieved

2.3 Routine Prophylaxis

The dose for previously treated patients (PTPs) is 60 to 80 international units per kg twice weekly for patients <12 years of age and is 40 to 60 international units per kg twice weekly for patients ≥12 years of age. Adjust the dose based on the individual patient's age, bleeding pattern, and physical activity.

2.4 Preparation and Reconstitution

The procedures below are provided as general guidelines for the preparation and reconstitution of RIXUBIS. Always work on a clean surface and wash hands before performing the following procedures:

1. Use aseptic technique during reconstitution procedure.
2. Allow the RIXUBIS vial (dry factor concentrate) and Sterile Water for Injection, USP vial (diluent) to reach room temperature.
3. Remove caps from the factor concentrate and diluent vials.
4. Cleanse stoppers with germicidal solution and allow the stopper to dry prior to use. Place the vials on a flat surface.
5. Open the BAXJECT® II device package by peeling away the lid, without touching the inside (Figure A). Do not remove the device from the package. Note that the BAXJECT II device is intended for use with a single vial of RIXUBIS and Sterile Water for Injection, USP only; therefore, reconstituting and withdrawing a second vial into the syringe requires a second BAXJECT II device.
6. Turn the package over. Press straight down to fully insert the clear plastic spike through the diluent vial stopper (Figure B).
7. Grip the BAXJECT II package at its edge and pull the package off the device (Figure C). Do not remove the blue cap from the BAXJECT II device. Do not touch the exposed white plastic spike.
8. Turn the system over so that the diluent vial is on top. Quickly insert the white plastic spike fully into the RIXUBIS vial stopper by pushing straight down (Figure D). The vacuum will draw the diluent into the RIXUBIS vial.
9. Swirl gently until the powder is completely dissolved. Do not refrigerate after reconstitution. Use within 3 hours of reconstitution.

2.5 Administration

For intravenous bolus infusion only.

- The safety and efficacy of RIXUBIS administration by continuous infusion has not been established.
- Inspect parenteral drug products for particulate matter and discoloration prior to administration. The solution should be clear and colorless in appearance. Do not use RIXUBIS if you notice any particulates or turbidity in the solution and notify Takeda Pharmaceuticals.
- Perform product administration and handling of the administration set and needles with caution. Percutaneous puncture with a needle contaminated with blood can transmit infectious viruses including HIV (AIDS) and hepatitis. Obtain immediate medical attention if injury occurs. Place needles in a sharps container after single-use.
- Administer RIXUBIS at room temperature and within 3 hours of reconstitution. Discard any unused product.

1. Use a plastic syringe with this product.
2. Remove the blue cap from the BAXJECT II device. Connect the syringe to the BAXJECT II device by screwing it clockwise until the syringe is secured (Figure E). Do not over tighten.
3. Do not inject air.
4. Turn the system upside down (factor concentrate vial now on top). Draw the factor concentrate into the syringe by pulling the plunger back slowly (Figure F).
5. Disconnect the syringe by unscrewing it counterclockwise; attach a suitable needle to the syringe and inject intravenously by bolus infusion. If a patient is to receive more than one vial of RIXUBIS, the contents of multiple vials may be drawn into the same syringe.
6. Maximum infusion rate of 10 mL/min.

Figure A

Figure B

Figure C

Figure D

Figure E

Figure F

3 DOSAGE FORMS AND STRENGTHS

RIXUBIS is a white or almost white lyophilized powder in single-dose vials containing nominally 250, 500, 1000, 2000, or 3000 international units.

4 CONTRAINDICATIONS

RIXUBIS is contraindicated in patients who have:

- Known hypersensitivity to RIXUBIS or its excipients including hamster protein
- Disseminated Intravascular Coagulation (DIC) [see Warnings and Precautions (5.4)]
- Signs of fibrinolysis [see Warnings and Precautions (5.4)]

5 WARNINGS AND PRECAUTIONS

5.1 Hypersensitivity Reactions

Hypersensitivity reactions have been reported with RIXUBIS. Anaphylaxis and other hypersensitivity reactions are possible. The risk is highest during the early phases of initial exposure in previously untreated patients (PUPs), in particular in patients with high-risk gene mutations. Early signs of allergic reactions, which can progress to anaphylaxis, include angioedema, chest tightness, hypotension, lethargy, nausea, vomiting, paresthesia, restlessness, wheezing, and dyspnea. Immediately discontinue administration and initiate appropriate treatment if allergic- or anaphylactic-type reactions occur. In case of severe allergic reactions, alternative hemostatic measures should be considered.

There have been reports in the literature showing an association between the occurrence of a factor IX inhibitor and allergic reactions. Evaluate patients experiencing allergic reactions for the presence of an inhibitor.

RIXUBIS contains trace amounts of Chinese hamster ovary (CHO) proteins. Patients treated with this product may develop hypersensitivity to these non-human mammalian proteins.

5.2 Inhibitors

Evaluate patients regularly for the development of factor IX inhibitors by appropriate clinical observations and laboratory tests. Perform an assay that measures factor IX inhibitor concentration if expected factor IX activity plasma levels are not attained, or if bleeding is not controlled with an expected dose. Contact a specialized hemophilia treatment center if a patient develops an inhibitor.

Patients with factor IX inhibitors are at an increased risk of severe hypersensitivity reactions or anaphylaxis if re-exposed to RIXUBIS. RIXUBIS may not be effective in patients with high titer factor IX inhibitors and other therapeutic options should be considered.

5.3 Nephrotic Syndrome

Nephrotic syndrome has been reported following attempted immune tolerance induction in hemophilia B patients with factor IX inhibitors. The safety and efficacy of using RIXUBIS for immune tolerance induction have not been established.

5.4 Thromboembolic Complications

The use of factor IX-containing products has been associated with the development of thromboembolic complications (e.g., pulmonary embolism, venous thrombosis, and arterial thrombosis). Due to the potential risk for thromboembolic complications, monitor patients for early signs of thromboembolic and consumptive coagulopathy, when administering RIXUBIS to patients with liver disease, with signs of fibrinolysis, peri- and post-operatively, or at risk for thromboembolic events or DIC. The benefit of treatment with RIXUBIS should be weighed against the risk of these complications in patients with DIC or those at risk for DIC or thromboembolic events.

5.5 Monitoring Laboratory Tests

- Monitor factor IX activity plasma levels by the one-stage clotting assay to confirm that adequate factor IX levels have been achieved and maintained [see Dosage and Administration (2)].
- Monitor for the development of inhibitors if expected factor IX activity plasma levels are not attained, or if bleeding is not controlled with the recommended dose of RIXUBIS. Assays used to determine if factor IX inhibitor is present should be titered in Bethesda Units (BUs).

6 ADVERSE REACTIONS

Common adverse reactions observed in >1% of subjects in clinical studies were dysgeusia, pain in extremity, and positive furin antibody test.

6.1 Clinical Trials Experience

Because clinical trials are conducted under widely varying conditions, adverse reaction rates observed in the clinical trials of a drug cannot be directly compared to rates in the clinical trials of another drug and may not reflect the rates observed in clinical practice.

During clinical development, in a combined trial, 99 male previously treated patients (PTPs; exposed to a factor IX-containing product for ≥150 days) received at least one infusion of RIXUBIS as part of either on-demand treatment of bleeding episodes, perioperative management of major and minor surgical, dental, or other invasive procedures, routine prophylaxis, or pharmacokinetic evaluation of RIXUBIS. Eleven subjects (11.1%) were <6 years of age, 12 (12.1%) were 6 to <12 years of age, 3 (3%) were adolescents (12 to <16 years of age), and 73 (73.7%) were adults (16 years of age and older). The subjects received a total of 14,018 infusions with a median of 163 infusions of RIXUBIS (range 8 to 327 infusions), for a median of 156 exposure days (range 8 to 316 days).

A total of 337 adverse events were reported in 80 (80.8%) of the 99 subjects. Adverse reactions that occurred in >1% of subjects are shown in Table 3.

Table 3 Summary of Adverse Reactions
System Organ Class | Adverse Reactions (AR) | Number of ARs (N) | Number of Subjects (N=99) n (%) | Percent per Infusion (N=14,018)
Nervous System Disorders | Dysgeusia | 2 | 1 (1.01%) | 0.014%
Musculoskeletal and Connective Tissue Disorders | Pain in extremity | 1 | 1 (1.01%) | 0.007%
Investigations | Positive furin antibody test [See Immunogenicity.] | 2 | 2 (2.02%) | 0.014%

Immunogenicity

All 99 subjects were monitored for inhibitory and binding antibodies to factor IX, and binding antibodies to CHO protein and furin, at the following time points: at screening, at 72 hours following the first infusion of RIXUBIS and the commercial recombinant factor IX product in the crossover portion of the pharmacokinetic trial, after 5 and 13 weeks following first exposure to RIXUBIS, and thereafter every 3 months. Antibodies against furin were tested by an in-house enzyme-linked immunosorbent assay (ELISA). A titer of 1:20 or 1:40 was considered to be indeterminate for the above validated assay, as these titers were too low to be verified by the confirmatory assay.

No subjects developed neutralizing antibodies to factor IX. Low-titer, non-neutralizing antibodies against factor IX were observed in 21 (21.2%) subjects at one or more time points. Three of these 21 subjects were found to have these antibodies at screening, prior to receiving RIXUBIS. Six of the 21 subjects were pediatric (2 subjects in <6 years of age cohort, 4 subjects in 6 to <12 years age cohort). No clinical adverse findings were observed in any of these 21 subjects.

Nineteen subjects (19.2%) had signals for antibodies against furin (indeterminate specificity). Five of these 19 subjects expressed signals for antibodies at screening, prior to RIXUBIS treatment. One subject had an antibody signal after treatment with the comparator product and prior to RIXUBIS treatment. Two additional subjects had a positive titer of 1:80 that was not present when checked at a later time point and therefore considered transient. Two of the 19 subjects were pediatric (6 to <12 years age cohort). All post-treatment antibody titer increases in these two pediatric subjects were <2 dilution steps and therefore considered unrelated to treatment. No clinical adverse findings were observed in any of these 19 subjects.

In a trial of 500 normal volunteers, using the same assay as in the clinical trial, 7% had titers of 1:20 or 1:40 and 1.2% had higher titers ranging from 1:80 to 1:320. These antibodies are thought to be part of a natural immune system response. To date, these antibodies have not been associated with any clinical adverse findings.

The detection of antibody formation is dependent on the sensitivity and specificity of the assay. Additionally, the observed incidence of antibody (including neutralizing antibody) positivity in an assay may be influenced by several factors, including assay methodology, sample handling, timing of sample collection, concomitant medications, and underlying disease.

Thrombogenicity

There was no clinical evidence of thromboembolic complications in any of the subjects. Out-of-range values for thrombogenicity markers (thrombin-antithrombin III, prothrombin fragment 1.2, and D-dimer), determined during the pharmacokinetic portion of the combined trial, did not reveal any pattern indicative of clinically relevant thrombogenicity with either RIXUBIS or a comparator factor IX-containing product.

6.2 Postmarketing Experience

The following adverse reactions have been identified during post-approval use of RIXUBIS. Because the following reactions are reported voluntarily from a population of uncertain size, it is not always possible to reliably estimate their frequency or establish a causal relationship to drug exposure.

Immune System Disorders: Hypersensitivity (including symptoms such as dyspnea, pruritus)

Skin and Subcutaneous Tissue Disorders: Urticaria, rash

The following class adverse reactions have been seen with another recombinant factor IX: inadequate factor IX recovery, inhibitor development, anaphylaxis, angioedema, hypotension, and thrombosis.

8 USE IN SPECIFIC POPULATIONS

8.1 Pregnancy

Risk Summary

There are no data with RIXUBIS use in pregnant women to inform a drug-associated risk. Animal reproduction studies have not been conducted with RIXUBIS. It is also not known whether RIXUBIS can cause fetal harm when administered to a pregnant woman or can affect reproduction capacity.

In the U.S. general population, the estimated background risk of major birth defects and miscarriages in clinically recognized pregnancies is 2-4% and 15-20%, respectively, regardless of drug exposure.

8.2 Lactation

Risk Summary

There is no information regarding the presence of RIXUBIS in human milk, the effect on the breastfed infant, or the effects on milk production.

The developmental and health benefits of breastfeeding should be considered along with the mother's clinical need for RIXUBIS and any potential adverse effects on the breastfed child from RIXUBIS or from the underlying maternal condition.

8.4 Pediatric Use

Safety, efficacy and pharmacokinetics of RIXUBIS have been evaluated in 23 previously treated pediatric patients. Twelve (52.2%) were 6 to <12 years of age and 11 subjects (47.8%) were <6 years of age. Previously treated pediatric subjects 6 to <12 years of age were previously treated with plasma-derived and/or recombinant factor IX concentrate(s) for a minimum of 150 exposure days (based on the subject's medical records). Subjects <6 years of age were previously treated with plasma-derived and/or recombinant factor IX concentrate(s) for > 50 exposure days (based on the subject's medical records).

Incremental recovery was observed to be 22% lower in pediatric patients (<12 years) and dose adjustment is needed [see Dosage and Administration (2) and Clinical Pharmacology (12.3)]. The mean incremental recovery (in [IU/dL]/[IU/kg]) at the initial pharmacokinetics evaluation was 0.67 (± 0.16) in subjects of both age cohorts, with lower values in the younger age cohort (0.59 ± 0.13) and higher values in the older age group (0.73 ± 0.16). Clearance was higher in the younger age cohort, with a mean clearance of 10.6 ± 1.7 mL/(kg.hr) (median: 10.5; range: 8.1-14.4) in the <6 years age cohort compared to a mean clearance of 8.7 ± 1.2 mL/(kg.hr) (median: 8.6; range: 6.9-10.8) in the 6 to <12 years age cohort.

In a prospective, open-label, uncontrolled multicenter trial with patients <12 years of age, a total of 41 infusions were given for the treatment of 26 bleeding episodes (7 joint, 19 muscle and soft tissue). Bleeding was controlled in all episodes. In 23 of 26 (88.5%) of the episodes, hemostasis was achieved with one or two infusions. The mean annualized bleeding episode rate (ABR) for children <12 years of age was 2.7 bleeds per patient per year ± 3.14 with a median of 2 ranging from 0 to 10.8. See Clinical Studies (14) for patients 12 to <16 years of age. The median ABR during prophylaxis was comparable among children, adolescents and adults.

8.5 Geriatric Use

Clinical studies of RIXUBIS did not include subjects aged 65 and over. It is not known whether elderly patients respond differently than younger patients. Dose selection for an elderly patient should be individualized [see Dosage and Administration (2)].

11 DESCRIPTION

RIXUBIS [Coagulation Factor IX (Recombinant)] is a purified protein produced by recombinant DNA technology. Its amino acid sequence is identical to that of the Ala-148 allelic form of plasma derived factor IX, and its structural and functional characteristics are similar to those of plasma derived factor IX. RIXUBIS is produced by a genetically engineered CHO cell line. No human or animal proteins are added during any stage of manufacturing or formulation of RIXUBIS. The CHO cell line secretes recombinant factor IX into a defined cell culture medium that does not contain hormones, and the recombinant factor IX is purified by a chromatography purification process that does not require a monoclonal antibody step. The process includes validated virus inactivation/removal steps, namely solvent/detergent treatment and 15 nm nanofiltration. RIXUBIS is predominantly a single component by sodium dodecyl sulfate-polyacrylamide gel electrophoresis evaluation. The specific activity of RIXUBIS is ≥200 international units per milligram of protein. Factor IX preactivation, the percent of Factor IXa/Factor IX as measured by activity assays, is ≤0.03%. The potency in international units is determined using an in vitro thromboplastin time (aPTT)-based one-stage clotting assay calibrated against the World Health Organization (WHO) International Standard for Factor IX concentrate. Factor IX potency results can be affected by the type of aPTT reagent and reference standard used in the assay; differences of up to 40% have been observed.

RIXUBIS is formulated as a sterile, nonpyrogenic lyophilized powder to be reconstituted with Sterile Water for Injection for intravenous administration. It does not contain any preservatives and is available in single-dose vials containing the labeled amount of factor IX activity, expressed in international units. Each vial contains nominally 250, 500, 1000, 2000, or 3000 international units of recombinant coagulation factor IX. After reconstitution of the lyophilized powder, all dosage strengths yield a clear, colorless solution. The concentrations of excipients are shown in Table 4:

Table 4 Concentrations of excipients
Excipient | Concentration
L-histidine | 20 mM
Sodium chloride | 60 mM
Calcium chloride | 4 mM
Mannitol | 110 mM
Sucrose | 35 mM
Polysorbate 80 | 0.005%

12 CLINICAL PHARMACOLOGY

12.1 Mechanism of Action

Patients with hemophilia B are deficient in coagulation factor IX, which is required for effective hemostasis. Treatment with RIXUBIS temporarily replaces the missing coagulation factor IX.

12.2 Pharmacodynamics

The administration of RIXUBIS increases plasma levels of factor IX and can temporarily correct the coagulation defect in these patients by decreasing the aPTT.

12.3 Pharmacokinetics

PTPs ≥12 Years of Age

A randomized, blinded, controlled pharmacokinetic trial of RIXUBIS was conducted in non-bleeding subjects (≥15 years of age). The subjects received RIXUBIS as an intravenous infusion. The infusion rate for the first administration during the trial was not to exceed 4 mL/minute with a maximum infusion rate of 10 mL/minute. The dose range of RIXUBIS was from 71.3 to 79.4 international units/kg (mean dose = 74.7 international units/kg). Blood samples for factor IX activity measurements were obtained up to 72 hours and a non-compartmental analysis was used to estimate pharmacokinetic parameters.

The pharmacokinetic evaluation was repeated for RIXUBIS in a prospective, open-label, uncontrolled trial with RIXUBIS in subjects who participated in the initial trial and had then received RIXUBIS for 26 ± 1 (mean ± SD) weeks for routine prophylaxis and accumulated at least 30 exposure days to RIXUBIS. The dose range of RIXUBIS in this repeat pharmacokinetic trial was 64.5 to 79.2 international units/kg (mean dose = 74.6 international units/kg). Table 5 presents the pharmacokinetic parameters for all evaluable subjects (per protocol analysis).

Table 5 Pharmacokinetic Parameters for RIXUBIS Following Single and Repeat Dosing (≥12 years of age)
Parameter | First Dose (N=25) | Repeat Dose (N=23)
AUC0-inf (IU∙hrs/dL) [Area under the plasma concentration-time curve from time 0 to infinity hours post-infusion.]
Mean (SD) | 1207 (242) | 1305 (300)
Min; Max | 850; 1710 | 838; 1864
Incremental recovery at Cmax (IU/dL:IU/kg) [Calculated as (Cmax – baseline factor IX) divided by the dose in IU/kg, where Cmax is the maximum post-infusion factor IX measurement.]
Mean (SD) | 0.87 (0.22) | 0.95 (0.25)
Min; Max | 0.53; 1.35 | 0.52; 1.38
Half-life (hrs)
Mean (SD) | 26.7 (9.6) | 25.4 (6.9)
Min; Max | 15.8; 52.3 | 16.2; 42.2
Cmax (IU/dL)
Mean (SD) | 66.2 (15.8) | 72.7 (19.7)
Min; Max | 41.7; 100.3 | 38.5; 106.3
Mean Residence Time (hrs)
Mean (SD) | 30.8 (7.3) | 29.9 (4.2)
Min; Max | 22.3; 47.8 | 21.3; 37.5
VSS [Volume of distribution at steady state.] (mL/kg)
Mean (SD) | 201.9 (77.4) | 178.6 (45.2)
Min; Max | 110.0; 394.0 | 112.0; 272.0
Clearance [mL/(kg∙hr)]
Mean (SD) | 6.4 (1.3) | 6.0 (1.5)
Min; Max | 4.3; 9.1 | 4.1; 9.5

Data from PTPs who underwent repeat in vivo recovery testing for up to 26 weeks demonstrated that the incremental factor IX recovery was consistent over time (Table 6).

Table 6 Incremental Recovery for RIXUBIS 30 Minutes After Infusion (≥12 years of age)
Incremental recovery 30 min after infusion (IU/dL:IU/kg) [Calculated as (C30min – baseline factor IX) divided by the dose in IU/kg, where C30min is the factor IX measurement 30 minutes after infusion.] | Day 1 (N=73) | Week 5 (N=71) | Week 13 (N=68) | Week 26 (N=55) | At trial completion/termination [If not coinciding with week 26 visit.] (N=23)
Incremental recovery 30 min after infusion (IU/dL:IU/kg) [Calculated as (C30min – baseline factor IX) divided by the dose in IU/kg, where C30min is the factor IX measurement 30 minutes after infusion.] | Mean ± SD | 0.79 ± 0.20 | 0.83 ± 0.21 | 0.85 ± 0.25 | 0.89 ± 0.12 | 0.87 ± 0.20
Median (range) | 0.78 (0.26-1.35) | 0.79 (0.46-1.48) | 0.83 (0.14-1.47) | 0.88 (0.52-1.29) | 0.89 (0.52-1.32)

PTPs <12 Years of Age

Twenty-three male subjects underwent a pharmacokinetic evaluation of RIXUBIS as part of the combined pediatric trial (<6 years and 6 -<12 years). The mean (± SD) and median dose were 75.5 ± 3.0 and 75.3 international units/kg, respectively, with a range of 70.0 to 83.6 international units/kg. Non-linear mixed model (population PK) was used to estimate the pharmacokinetic parameters from factor IX activity measurements in blood samples obtained up to 60 hours following the infusion. Pharmacokinetic parameters for all subjects are presented in Table 7.

Table 7 Pharmacokinetic Parameters for PTPs
Parameter | ≥12 years [Non-linear mixed model (population PK) was applied on the reduced 4 blood samples (30min, 6hr, 24hr, and 60hr).] (N=25) | 6 - <12 years (N=12) | <6 years (N=11)
AUC0–inf (IU∙hr/dL)
Mean ± SD | 1185 ± 273 | 886 ± 134 | 724 ± 119
Median (range) | 1197 (783-1780) | 864 (730-1138) | 717 (488-947)
Half-life (hr)
Mean ± SD | 25.7 ± 1.5 | 23.2 ± 1.6 | 27.7 ± 2.7
Median (range) | 25.6 (22.8-29.0) | 22.6 (21.8-27.4) | 27.3 (24.0-32.2)
Mean residence time (hr)
Mean ± SD | 30.2 ± 2.2 | 25.3 ± 1.8 | 30.6 ± 3.3
Median (range) | 30.3 (25.9-33.9) | 24.7 (23.7-30.3) | 30.1 (26.2-36.2)
VSSb (mL/kg)
Mean ± SD | 201.5 ± 47.2 | 220.9 ± 31.7 | 322.5 ± 52.3
Median (range) | 190.2 (138-300) | 218.5 (169.9-270.1) | 315.7 (264.7-441.5)
Clearance (mL/[kg∙hr])
Mean ± SD | 6.7 ± 1.5 | 8.7 ± 1.2 | 10.6 ± 1.7
Median (range) | 6.43 (4.1-9.9) | 8.6 (6.9-10.8) | 10.5 (8.1-14.4)

Incremental recovery 30 minutes after infusion was determined for all subjects in the combined trial during the pharmacokinetic evaluation (exposure day 1), at week 5, 13, and 26 visits, and at the time of trial completion or termination, if it did not coincide with the week 26 visit. The data demonstrate that the incremental recovery is consistent over time across all pediatric age groups. (see Tables 8 and 9)

Table 8 Incremental Recovery for RIXUBIS 30 Minutes After Infusion Ages < 6 Years
Incremental recovery 30 min after infusion | PK (ED 1) (N=10) | Week 5 (N=11) | Week 13 (N=10) | Week 26 (N=10)
(IU/dL÷IU/kg) [Calculated as (C30min–baseline factor IX) divided by the dose in IU/kg, where C30min is the factor IX measurement 30 minutes after infusion.]
Mean ± SD | 0.59 ± 0.13 | 0.63 ± 0.10 | 0.68 ± 0.12 | 0.65 ± 0.13
Median (range) | 0.59 (0.31-0.75) | 0.6 (0.49-0.80) | 0.66 (0.51-0.84) | 0.61 (0.51-0.84)

Table 9 Incremental Recovery for RIXUBIS 30 Minutes After Infusion Ages 6 - <12 Years
Incremental recovery 30 min after infusion | PK (ED 1) N=12) | Week 5 (N=12) | Week 13 (N=11) | Week 26 (N=11)
(IU/dL÷IU/kg) [Calculated as (C30min–baseline factor IX) divided by the dose in IU/kg, where C30min is the factor IX measurement 30 minutes after infusion.]
Mean ± SD | 0.73 ± 0.16 | 0.73 ± 0.13 | 0.73 ± 0.14 | 0.8 ± 0.14
Median (range) | 0.71 (0.51 – 1.00) | 0.70 (0.48-0.92) | 0.70 (0.54-1.00) | 0.78 (0.56-1.01)

13 NONCLINICAL TOXICOLOGY

13.1 Carcinogenesis, Mutagenesis, Impairment of Fertility

Nonclinical studies evaluating the carcinogenic and mutagenic potential of RIXUBIS have not been conducted.

No adverse effects on reproductive organs were observed by macroscopic and microscopic pathological investigations in repeated dose toxicity studies. No investigations on impairment of fertility have been conducted.

14 CLINICAL STUDIES

On-demand Treatment of Bleeding Episodes in PTPs ≥12 Years of Age

A total of 249 bleeding episodes were treated with RIXUBIS, of which 115 bleeds were recorded for subjects treated on prophylaxis and 134 bleeds for those with the on-demand regimen. There were 197 joint bleeds and 52 non-joint bleeds (soft tissue, muscle, body cavity and other). Of the 249 bleeding episodes, 15 were major, 163 were moderate, and 71 were minor (see Table 1 for definitions of major, moderate and minor). Treatment was individualized based on the severity, cause, and site of bleed. The majority (211; 84.7%) were treated with 1 to 2 infusions. Of these, 153 (61.4%) were treated with 1 infusion and 58 (23.3%) were treated with 2 infusions. No non-responders were reported.

Hemostatic efficacy at resolution of a bleed was rated excellent or good in 96% of all treated bleeding episodes. (Excellent is defined as full relief of pain and cessation of objective signs of bleeding after a single infusion; no additional infusion is required for the control of bleeding; Good is defined as definite pain relief and/or improvement in signs of bleeding after a single infusion; possibly requires more than one infusion for complete resolution).

On-demand Treatment of Bleeding Episodes in PTPs <12 Years of Age

A total of 26 bleeding episodes were treated with RIXUBIS, of which 23 bleeds were due to injury, 2 spontaneous and 1 of unknown origin; 19 bleeds were non-joint (soft tissue, muscle, body cavity, intracranial and other) and 7 were joint bleeds of which 1 was a bleed into a target joint. Of the 26 bleeding episodes, 15 were minor, 9 moderate, and 2 major (Minor: little or no pain; little or no change in the range of motion of affected joint (if joint bleeding event); mild restriction of mobility and activity; Moderate: mild to moderate pain; some decrease in range of motion of affected joint (if joint bleeding event); moderate decrease in mobility and activity; Major/life threatening: significant pain; substantial decrease in range of motion of affected joint (if joint bleeding event); incapacity; life threatening). Treatment was individualized based on the severity, cause and site of bleed. The majority (23; 88.5%) were treated with 1 to 2 infusions. Of the treated bleeding episodes 15 (57.7%) received 1 infusion, 8 (30.8%) received 2 infusions, and 3 (11.5%) were treated with 3 infusions. Hemostatic efficacy at resolution of a bleed was rated excellent or good in 96.2% of all treated bleeding episodes.

Perioperative Management

The efficacy analysis of RIXUBIS in perioperative management included 14 surgeries performed in 14 PTPs between 19 and 54 years of age undergoing major or minor surgical (see Table 2 for definitions of major and minor), dental or other surgical invasive procedures. Eleven procedures (including 7 orthopedic and 1 dental surgeries) were major, 3 procedures (including 2 dental extractions) were minor.

Subjects undergoing major surgeries also underwent a pharmacokinetic evaluation. All subjects were dosed based on their most recent individual incremental recovery. The recommended initial loading dose of RIXUBIS was used to ensure that during surgery factor IX activity levels of 80-100% for major surgeries and 30-60% for minor surgeries were maintained. RIXUBIS was administered by intravenous bolus infusions. Hemostasis was maintained throughout the trial duration. The following are the surgical procedures and results of the assessment of the hemostatic response at various points.

Fourteen surgeries (11 major; 3 minor), included in the intraoperative assessment had a rating of 'excellent'. At discharge from hospital 11/14 surgeries (8 major) had a rating of 'excellent' and 3/14 (3 major) had a rating of 'good'.

The rating of excellent, good, fair and none at 72 hours post-surgery was based on the hemostasis achieved as compared to that expected in hemostatically normal subjects.

Routine Prophylaxis and Control of Bleeding in PTPs ≥12 Years of Age

The efficacy of RIXUBIS has been evaluated in a prospective, open-label, uncontrolled multicenter trial, in which a total of 73 male PTPs between 12 and 65 years of age received RIXUBIS either for routine prophylaxis or on-demand treatment. In addition, there is an ongoing prospective, open-label, uncontrolled, multicenter trial where 14 PTPs underwent minor or major surgeries receiving RIXUBIS for perioperative management. PTPs were defined as subjects who were exposed to a factor IX containing product for ≥150 days. All subjects had severe (factor IX level <1%) or moderately severe (factor IX level ≤2%) hemophilia B. The majority of subjects (88%) had arthropathy and/or target joints (66%) at screening. Subjects with history of a detectable factor IX inhibitor ≥0.6 BU, history of severe allergic reactions following exposure to factor IX containing products, evidence of severe chronic liver disease (INR >1.4), impaired renal function, CD4 count <200 cells/mm^3, or any hemostatic defect other than hemophilia B, were excluded from the trial.

Of 59 subjects who received RIXUBIS for routine prophylaxis, 56 subjects received the product for a minimum of 3 months and were included in the efficacy evaluation. The prophylactic regimen consisted of 40 to 60 international units/kg RIXUBIS twice weekly. An additional 14 subjects received RIXUBIS on-demand for treatment of bleeding episodes only. These subjects had to have at least 12 documented bleeding episodes requiring treatment within 12 months prior to enrollment.

In the on-demand arm, the mean treatment duration was 3.5 ± 1 months (median 3.4, ranging from 1.2 to 5.1 months) and the mean total annualized bleeding rate (ABR was 33.9 ± 17.37 with a median of 27 ranging from 12.9 to 73.1).

In the prophylaxis arm the mean ABR was 4.3 for all bleeds, 1.7 for spontaneous bleeds, and 2.9 for joint bleeds (Table 10).

Table 10 Efficacy of Routine Prophylaxis with RIXUBIS (N=56) ≥12 Years of Age
Total ABR
Mean ± SD | 4.3 ± 5.80
Median (range) | 2.0 (0.0-23.4)
ABR for joint bleeds
Mean ± SD | 2.9 ± 4.25
Median (range) | 0.0 (0.0-21.5)
ABR for spontaneous bleeds
Mean ± SD | 1.7 ± 3.26
Median (range) | 0.0 (0.0-15.6)
Subjects with zero bleeding episodes
% (n) | 42.9% (24)
*The prophylactic regimen consisted of 40 to 60 international units/kg RIXUBIS twice weekly.

Routine Prophylaxis and Control of Bleeding in PTPs <12 Years of Age

The efficacy of RIXUBIS has been evaluated in a clinical trial, in which a total of 23 male, (PTPs) between 1.8 and 11.8 years (median age 7.10 years) with 11 subjects <6 years, received RIXUBIS for prophylaxis and control of bleeding episodes. PTPs were defined as subjects who were exposed to a factor IX-containing product on ≥150 days for subjects aged 6 to <12 years and on ≥50 days for subjects aged <6 years. All subjects had severe (factor IX level <1%) or moderately severe (factor IX level ≤2%) hemophilia B. Subjects with a history of or a detectable FIX inhibitor ≥0.6 BU, a history of severe allergic reactions following exposure to FIX, evidence of severe chronic liver disease (INR >1.4), impaired renal function, a CD4 count <200 cells/mm^3 or any hemostatic effect other than hemophilia B were excluded from participation. All 23 subjects received prophylactic treatment with RIXUBIS for a minimum of 3 months and were included in the efficacy evaluation for prophylaxis (see Table 11).

Table 11 Efficacy of Routine Prophylaxis of RIXUBIS in 23 PTPs <12 Years of Age
Total annualized bleeding rate (ABR)
Mean ± SD | 2.7 ± 3.14
Median (range) | 2.0 (0.0–10.8)
ABR for joint bleeds
Mean ± SD | 0.8 ± 1.76
Median (range) | 0.0 (0.0–7.2)
ABR for spontaneous bleeds
Mean ± SD | 0.2 ± 0.66
Median (range) | 0.0 (0.0–2.0)
Subjects with zero bleeds
% (n) | 39.1.% (9)
* The prophylactic regimen consisted of 40 to 80 international units/kg RIXUBIS twice weekly.

15 REFERENCES

1. Roberts HR, Eberst ME. Current management of hemophilia B. Hematol Oncol Clin North Am. 1993;7(6):1269-1280.

16 HOW SUPPLIED/STORAGE AND HANDLING

How Supplied

RIXUBIS is available as single-dose vials containing the following product strengths:

Color Code | Nominal Strength (international units) | Kit NDC
Light Blue | 250 | 0944-3026-02
Pink | 500 | 0944-3028-02
Green | 1000 | 0944-3030-02
Orange | 2000 | 0944-3032-02
Silver | 3000 | 0944-3034-02

Actual factor IX activity in international units is stated on the unit carton and vial label.

Each kit also contains 5 mL of Sterile Water for Injection and a BAXJECT II transfer device.

Not made with natural rubber latex.

Storage and Handling

- Store at refrigerated temperature [2°C to 8°C (36°F to 46°F)] or room temperature [not to exceed 30°C (86°F)] for up to 36 months. Do not freeze.
- Do not use beyond the expiration date printed on the carton or vial.

17 PATIENT COUNSELING INFORMATION

- Advise the patient to read the FDA-approved patient labeling (Patient Information and Instructions for Use).
- Advise patients to report any adverse reactions or problems following RIXUBIS administration to their physician or healthcare provider.
- Inform patients of the early signs of hypersensitivity reactions (including hives, generalized urticaria, chest tightness, wheezing, and hypotension) and anaphylaxis. Instruct patients to discontinue use of the product and contact their physician if these symptoms occur.
- Advise patients to contact their physician or treatment facility for further treatment and/or assessment if they experience a lack of a clinical response to factor IX replacement therapy, as in some cases this may be a manifestation of an inhibitor.
- Ask patients to follow the specific preparation and administration procedures provided by their physician.
- Inform patients to follow the recommendations in the FDA-approved patient labeling.

Takeda Pharmaceuticals U.S.A., Inc.
Cambridge, MA 02142
U.S. License No. 1898

RIXUBIS and BAXJECT are registered trademarks of Baxalta Incorporated.
Takeda and are registered trademarks of Takeda Pharmaceutical Company Limited.

©2025 Takeda Pharmaceutical Company Limited. All rights reserved.

Patient Information

RIXUBIS®
[Coagulation Factor IX (Recombinant)]

This leaflet summarizes important information about RIXUBIS. Please read it carefully before using this medicine. This information does not take the place of talking with your healthcare provider, and it does not include all of the important information about RIXUBIS. If you have any questions after reading this, ask your healthcare provider.

What is RIXUBIS?

RIXUBIS is a medicine used to replace clotting factor (Factor IX) that is missing in people with hemophilia B. Hemophilia B is also called congenital factor IX deficiency or Christmas disease. Hemophilia B is an inherited bleeding disorder that prevents blood from clotting normally. RIXUBIS is used to prevent and control bleeding in people with hemophilia B. Your healthcare provider may give you RIXUBIS when you have surgery. RIXUBIS can reduce the number of bleeding episodes when used regularly (prophylaxis).

Who should not use RIXUBIS?

You should not use RIXUBIS if you

- are allergic to hamsters
- are allergic to any ingredients in RIXUBIS.

Tell your healthcare provider if you are pregnant or breastfeeding because RIXUBIS may not be right for you.

What should I tell my healthcare provider before using RIXUBIS?

You should tell your healthcare provider if you

- have or have had any medical problems
- take any medicines, including prescription and non-prescription medicines, such as over-the-counter medicines, supplements or herbal remedies
- have any allergies, including allergies to hamsters
- are breastfeeding. It is not known if RIXUBIS passes into your milk and if it can harm your baby
- are pregnant or planning to become pregnant. It is not known if RIXUBIS may harm your unborn baby
- have been told that you have inhibitors to factor IX (because RIXUBIS may not work for you).

How should I infuse RIXUBIS?

RIXUBIS is given directly into the bloodstream. RIXUBIS should be administered as ordered by your healthcare provider. You should be trained on how to do infusions by your healthcare provider or hemophilia treatment center. Many people with hemophilia B learn to infuse their RIXUBIS by themselves or with the help of a family member.

Your healthcare provider will tell you how much RIXUBIS to use based on your weight, the severity of your hemophilia B, and where you are bleeding. You may have to have blood tests done after getting RIXUBIS to be sure that your blood level of factor IX is high enough to clot your blood. Call your healthcare provider right away if your bleeding does not stop after taking RIXUBIS.

What are the possible side effects of RIXUBIS?

Allergic reactions may occur with RIXUBIS. Call your healthcare provider or get emergency treatment right away if you get a rash or hives, itching, tightness of the throat, chest pain or tightness, difficulty breathing, lightheadedness, dizziness, nausea or fainting. Some common side effects of RIXUBIS were unusual taste in the mouth and limb pain. Tell your healthcare provider about any side effects that bother you or do not go away. These are not all the side effects possible with RIXUBIS. You can ask your healthcare provider for information that is written for healthcare professionals.

Your body may form inhibitors to factor IX. An inhibitor is part of the body's defense system. If you form inhibitors, it may stop RIXUBIS from working properly. Consult with your healthcare provider to make sure you are carefully monitored with blood tests for the development of inhibitors to factor IX.

What are the RIXUBIS dosage strengths?

RIXUBIS comes in five different dosage strengths: 250, 500, 1000, 2000, and 3000 international units. The actual strength will be imprinted on the label and on the box. The five different strengths are color coded, as follows:

Dosage strength of approximately 250 international units per vial

Dosage strength of approximately 500 international units per vial

Dosage strength of approximately 1000 international units per vial

Dosage strength of approximately 2000 international units per vial

Dosage strength of approximately 3000 international units per vial

Always check the actual dosage strength printed on the label to make sure you are using the strength prescribed by your healthcare provider.

How should I store RIXUBIS?

- Store at refrigerated temperature [2°C to 8°C (36°F to 46°F)] or room temperature [not to exceed 30°C (86°F)] for up to 36 months. Do not freeze.
- Do not use after the expiration date printed on the carton or vial.
- Reconstituted product (after mixing dry product with wet diluent) must be used within 3 hours and cannot be stored or refrigerated. Discard any RIXUBIS left in the vial at the end of your infusion.

What else should I know about RIXUBIS?

Medicines are sometimes prescribed for purposes other than those listed here. Do not use RIXUBIS for a condition for which it is not prescribed. Do not share RIXUBIS with other people, even if they have the same symptoms that you have.

Resources available to patients

For information on patient assistance programs that are available to you, please contact 1-888-229-8379.

Takeda Pharmaceuticals U.S.A., Inc.
Cambridge, MA 02142
U.S. License No. 1898

RIXUBIS and BAXJECT are registered trademarks of Baxalta Incorporated.
Takeda and are registered trademarks of Takeda Pharmaceutical Company Limited.

©2025 Takeda Pharmaceutical Company Limited. All rights reserved.

INSTRUCTIONS FOR USE

RIXUBIS®
[Coagulation Factor IX (Recombinant)]
For intravenous use only

Do not attempt to do an infusion to yourself unless you have been taught how by your healthcare provider or hemophilia center.

Always follow the specific instructions given by your healthcare provider. The steps listed below are general guidelines for using RIXUBIS. If you are unsure of the procedures, please call your healthcare provider before using RIXUBIS. Call your healthcare provider right away if bleeding is not controlled after using RIXUBIS. Your healthcare provider will prescribe the dose that you should take. Your healthcare provider may need to take blood tests from time to time. Talk to your healthcare provider before traveling. Plan to bring enough RIXUBIS for your treatment during this time. Dispose of all materials, including any leftover reconstituted RIXUBIS product, in an appropriate container.

1. Prepare a clean flat surface and gather all the materials you will need for the infusion. Check the expiration date, and let the vial with the RIXUBIS concentrate and the Sterile Water for Injection, USP (diluent) warm up to room temperature. Wash your hands and put on clean exam gloves. If infusing yourself at home, the use of gloves is optional.
2. Remove caps from the RIXUBIS concentrate and diluent vials to expose the centers of the rubber stoppers.
3. Disinfect the stoppers with an alcohol swab (or other suitable solution suggested by your healthcare provider or hemophilia center) by rubbing the stoppers firmly for several seconds and allow them to dry prior to use. Place the vials on a flat surface.
4. Open the BAXJECT® II device package by peeling away the lid, without touching the inside of the package. Do not remove the BAXJECT II device from the package.
5. Turn the package with the BAXJECT II device upside down and place it over the top of the diluent vial. Fully insert the clear plastic spike of the device into the center of the diluent vial stopper by pushing straight down. Grip the package at its edge and lift it off the device. Be careful not to touch the white plastic spike. Do not remove the blue cap from the BAXJECT II device. The diluent vial now has the BAXJECT II device connected to it and is ready to be connected to the RIXUBIS vial.
6. To connect the diluent vial to the RIXUBIS vial, turn the diluent vial over and place it on top of the vial containing RIXUBIS concentrate. Fully insert the white plastic spike into the RIXUBIS vial stopper by pushing straight down. Diluent will flow into the RIXUBIS vial. This should be done right away to keep the liquid free of germs.
7. Swirl the connected vials gently and continuously until the powder is completely dissolved. Do not shake. The RIXUBIS solution should look clear and colorless. If not, do not use it and notify Takeda Pharmaceuticals immediately.
8. Take off the blue cap from the BAXJECT II device and connect the syringe by screwing it clockwise until the syringe is secured. Do not over tighten. Be careful to not inject air.
9. Turn over the connected vials so that the RIXUBIS vial is on top. Draw the RIXUBIS solution into the syringe by pulling back the plunger slowly. Disconnect the syringe from the BAXJECT II unscrewing it counterclockwise.
10. If you are using more than one vial of RIXUBIS, the contents of more than one vial may be drawn into the same syringe. Make sure you mix each vial of RIXUBIS with the Sterile Water for Injection, USP that is provided in the box (following Steps 1-9). You will need a separate BAXJECT II device to mix each additional vial of RIXUBIS.
11. Attach the infusion needle to the syringe using a winged (butterfly) infusion set, if available. Point the needle up and remove any air bubbles by gently tapping the syringe with your finger and slowly and carefully pushing air out of the syringe and needle.
12. Apply a tourniquet and get the infusion site ready by wiping the skin well with an alcohol swab (or other suitable solution suggested by your healthcare provider or hemophilia center).
13. Insert the needle into the vein and remove the tourniquet. Slowly infuse the RIXUBIS. Do not infuse any faster than 10 mL per minute.
14. Take the needle out of the vein and use sterile gauze to put pressure on the infusion site for several minutes. Do not recap the needle. Place it with the used syringe in a hard-walled sharps container for proper disposal.
15. Dispose of the used vials and BAXJECT II system in your hard-walled sharps container without taking them apart. Do not dispose of these supplies in ordinary household trash.
16. Remove the peel-off label from the RIXUBIS vial and place it in your logbook. Clean any spilled blood with a freshly prepared mixture of 1 part bleach and 9 parts water, soap and water, or any household disinfecting solution.

Important: Contact your healthcare provider or local hemophilia treatment center if you experience any problems.

Takeda Pharmaceuticals U.S.A., Inc.
Cambridge, MA 02142
U.S. License No. 1898

RIXUBIS and BAXJECT are registered trademarks of Baxalta Incorporated.
Takeda and are registered trademarks of Takeda Pharmaceutical Company Limited.

©2025 Takeda Pharmaceutical Company Limited. All rights reserved.

Issue 3/2025

PRINCIPAL DISPLAY PANEL - Kit Carton - NDC 0944-3026-02

RIXUBIS®
[COAGULATION FACTOR IX
(RECOMBINANT)]

NDC 0944-3026-02

Single-dose Vial
Lyophilized Powder for Solution

For intravenous use after reconstitution.

Rx only

ACTUAL POTENCY

5
mL

Takeda

PRINCIPAL DISPLAY PANEL - 5 mL Vial Label - NDC 0944-3025-01

NDC 0944-3025-01

RIXUBIS®
[COAGULATION FACTOR IX
(RECOMBINANT)]

Rx Only

For Intravenous Use Only.

Directions for Use: See package insert.
Not made with natural rubber latex.

Takeda Pharmaceuticals U.S.A., Inc.
Cambridge, MA 02142
U.S. License No. 1898

Takeda

PRINCIPAL DISPLAY PANEL - Kit Carton - NDC 0944-3028-02

RIXUBIS®
[COAGULATION FACTOR IX
(RECOMBINANT)]

NDC 0944-3028-02

Single-dose Vial
Lyophilized Powder for Solution

For intravenous use after reconstitution.

Rx only

ACTUAL POTENCY

5
mL

Takeda

PRINCIPAL DISPLAY PANEL - 5 mL Vial Label - NDC 0944-3027-01

NDC 0944-3027-01

RIXUBIS®
[COAGULATION FACTOR IX
(RECOMBINANT)]

Rx Only

For Intravenous Use Only.

Directions for Use: See package insert.
Not made with natural rubber latex.

Takeda Pharmaceuticals U.S.A., Inc.
Cambridge, MA 02142
U.S. License No. 1898

Takeda

PRINCIPAL DISPLAY PANEL - Kit Carton - NDC 0944-3030-02

RIXUBIS®
[COAGULATION FACTOR IX
(RECOMBINANT)]

NDC 0944-3030-02

Single-dose Vial
Lyophilized Powder for Solution

For intravenous use after reconstitution.

Rx only

ACTUAL POTENCY

5
mL

Takeda

PRINCIPAL DISPLAY PANEL - 5 mL Vial Label - NDC 0944-3029-01

NDC 0944-3029-01

RIXUBIS®
[COAGULATION FACTOR IX
(RECOMBINANT)]

Rx Only

For Intravenous Use Only.

Directions for Use: See package insert.
Not made with natural rubber latex.

Takeda Pharmaceuticals U.S.A., Inc.
Cambridge, MA 02142
U.S. License No. 1898

Takeda

PRINCIPAL DISPLAY PANEL - Kit Carton - NDC 0944-3032-02

RIXUBIS®
[COAGULATION FACTOR IX
(RECOMBINANT)]

NDC 0944-3032-02

Single-dose Vial
Lyophilized Powder for Solution

For intravenous use after reconstitution.

Rx only

ACTUAL POTENCY

5
mL

Takeda

PRINCIPAL DISPLAY PANEL - 5 mL Vial Label - NDC 0944-3031-01

NDC 0944-3031-01

RIXUBIS®
[COAGULATION FACTOR IX
(RECOMBINANT)]

Rx Only

For Intravenous Use Only.

Directions for Use: See package insert.
Not made with natural rubber latex.

Takeda Pharmaceuticals U.S.A., Inc.
Cambridge, MA 02142
U.S. License No. 1898

Takeda

PRINCIPAL DISPLAY PANEL - Kit Carton - NDC 0944-3034-02

RIXUBIS®
[COAGULATION FACTOR IX
(RECOMBINANT)]

NDC 0944-3034-02

Single-dose Vial
Lyophilized Powder for Solution

For intravenous use after reconstitution.

Rx only

ACTUAL POTENCY

5
mL

Takeda

PRINCIPAL DISPLAY PANEL - 5 mL Vial Label - NDC 0944-3033-01

NDC 0944-3033-01

RIXUBIS®
[COAGULATION FACTOR IX
(RECOMBINANT)]

Rx Only

For Intravenous Use Only.

Directions for Use: See package insert.
Not made with natural rubber latex.

Takeda Pharmaceuticals U.S.A., Inc.
Cambridge, MA 02142
U.S. License No. 1898

Takeda